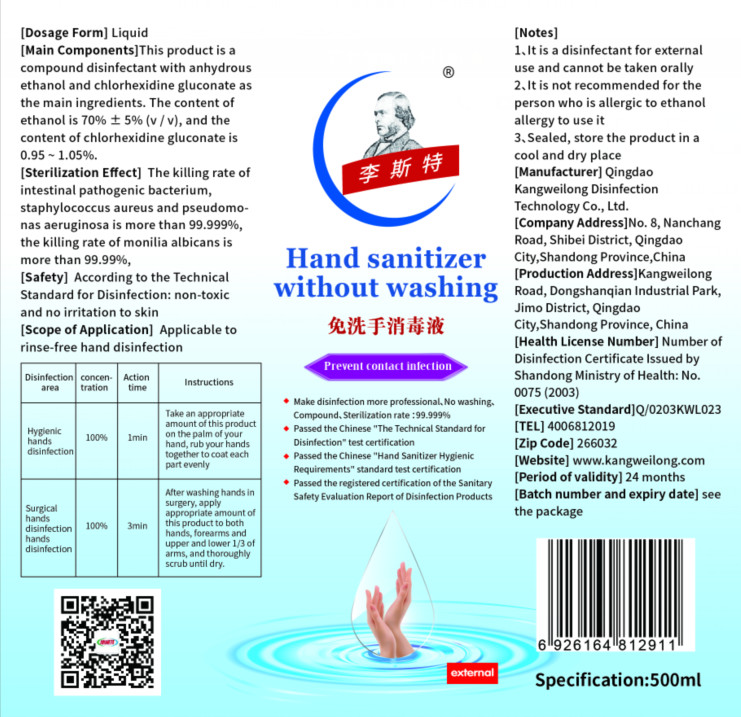 DRUG LABEL: Liszt Hand sanitizer without washing
NDC: 54529-003 | Form: LIQUID
Manufacturer: Qingdao Kangweilong Disinfection Technology Co.,Ltd.
Category: otc | Type: HUMAN OTC DRUG LABEL
Date: 20200514

ACTIVE INGREDIENTS: CHLORHEXIDINE GLUCONATE 5 g/500 mL; ALCOHOL 350 mL/500 mL
INACTIVE INGREDIENTS: WATER

DOSAGE AND ADMINISTRATION

Sealed, store the product in a cool and dry place.

INACTIVE INGREDIENT

pure water

INDICATIONS AND USAGE

Hygienic hands disinfection:Take an appropriate amount of this product on the palm of yourhand, rub your hands together tocoat each
part evenly in 1 min.

Surgical hands disinfection hands disinfection:Ater washing hands in surgery, apply appropriate amount of this product to both hands, forearms and upper and lower 1/3 of arms, and thoroughly scrub until dry in 3 min.

ACTIVE INGREDIENT

anhydrous ethanol

hlorhexidine gluconate

keep out of reach of children

PURPOSE

Disinfection
Sterilization
No Rinseing

WARNINGS

1.It is a disinfectant for external use and cannot be taken orally
2. It is not recommended for the person who is allergic to ethanol allergy to use it
3. Sealed, store the product in a cool and dry place